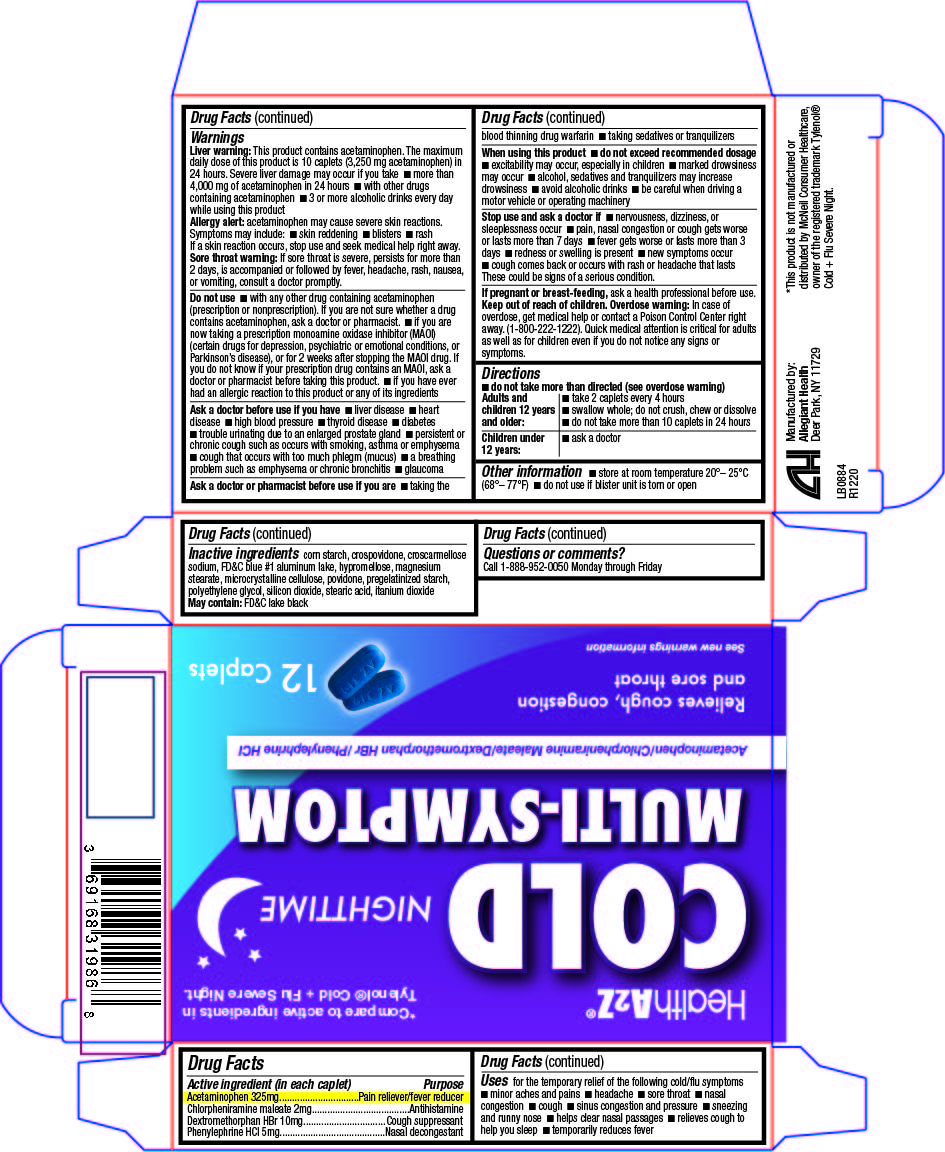 DRUG LABEL: Cold Multi-Symptom
NDC: 69168-319 | Form: TABLET
Manufacturer: Allegiant Health
Category: otc | Type: HUMAN OTC DRUG LABEL
Date: 20181226

ACTIVE INGREDIENTS: ACETAMINOPHEN 325 mg/1 1; CHLORPHENIRAMINE MALEATE 2 mg/1 1; DEXTROMETHORPHAN HYDROBROMIDE 10 mg/1 1; PHENYLEPHRINE HYDROCHLORIDE 5 mg/1 1
INACTIVE INGREDIENTS: SILICON DIOXIDE; STARCH, CORN; CROSCARMELLOSE SODIUM; FD&C BLUE NO. 1; MAGNESIUM STEARATE; CELLULOSE, MICROCRYSTALLINE; POVIDONE; STEARIC ACID; TITANIUM DIOXIDE; HYPROMELLOSE, UNSPECIFIED; POLYETHYLENE GLYCOL, UNSPECIFIED; CROSPOVIDONE

Drug Facts

Active ingredient

Acetaminophen 325 mg
Chlorpheniramine maleate 2 mg
Dextromethorphan HBr 10 mg
Phenylephrine HCI 5 mg

Purpose

Pain reliever/fever reducer
Antihistamine
Cough suppressant
Nasal decongestant

Uses

temporarily relieves these common cold/flu symptoms:

- minor aches and pains
- headache
- sore throat
- nasal congestion
- cough
- sneezing and runny nose
- sinus congestion and pressure
- helps clear nasal passages
- relieves cough to help you sleep
- temporarily reduces fever

Warnings

Liver warning/Allergy alert

Liver warning: This product contains acetaminophen. The maximum daily dose of this product is 10 caplets

(3,250 mg acetaminophen) in 24 hours. Severe liver damage may occur if you take

- more than 4,000 mg of acetaminophen in 24 hours with other drugs containing acetaminophen

- 3 or more alcoholic drinks every day while using this product

- with other drugs containing acetaminophen

Allergy alert: acetaminophen may cause severe skin reactions. Symptoms may include:

- skin reddening
- blisters
- rash

If a skin reaction occurs, stop use and seek medical help immediately

Sore throat warning: If sore throat is severe, persists for more than 2 days, is accompanied or followed by fever, headache, rash, nausea, or vomiting, consult a doctor promptly.

Do Not Use

- with any other drug containing acetaminophen (prescription or nonprescription). If you are not sure whether a drug
  contains acetaminophen, ask a doctor or pharmacist.
- if you are now taking a prescription monoamine oxidase inhibitor (MAOI)
  (certain drugs for depression, psychiatric or emotional conditions, or
  Parkinson’s disease), or for 2 weeks after stopping the MAOI drug. If
  you do not know if your prescription drug contains an MAOI, ask a
  doctor or pharmacist before taking this product.
- if you have ever had an allergic reaction to this product or any of its ingredients

Ask a doctor before use if you have

- liver disease
- heart disease
- high blood pressure
- thyroid disease
- diabetes
- trouble urinating due to an enlarged prostate gland
- persistent or chronic cough such as occurs with smoking, asthma, or emphysema
- cough that occurs with too much phlegm (mucus)

Ask a doctor or pharmacist before use if you are

- taking the blood thinning drug warfarin

- taking sedatives or tranquilizers

When using this product

do not exceed recommended dosage.

- excitability may occur, especially in children
- marked drowsiness may occur
- alcohol, sedatives and tranquilizers may increase drowsiness
- avoid alcoholic drinks
- be careful when driving a motor vehicle or operating machinery

Stop use and ask a doctor if

- nervousness, dizziness or sleeplessness occurs
- pain, nasal congestion or cough gets worse or lasts more than 7 days
- fever gets worse or lasts more than 3 days
- redness or swelling is present
- new symptoms occur
- cough comes back or occurs with rash or headache that lasts

These could be signs of a serious condition

If pregnant or breast-feeding

ask a health professional before use

Keep Out of Reach of Children

Overdose warning: In case of accidental overdose, contact a doctor or Poison Control Center (1-800-222-1222) immediately. Taking more than the recommended dose (overdose) may cause liver damage. Quick medical attention is critical for adults as well as for children even if you do not notice any signs or symptoms.

Directions

do not take more than directed (see Overdose Warnings)

Adults and children 12 years and over:

- take 2 caplets every 4 hours
- swallow whole; do not crush, chew or dissolve
- do not take more than a total of 10 caplets in 24 hours

Children under 12 years: ask a doctor

Other Information

- store at room temperature 20°– 25°C (68°– 77°F)
- do not use if blister is torn or open

Inactive Ingredients

corn starch, crospovidone, croscarmellose
sodium, FD&C blue #1 aluminum lake, hypromellose, magnesium
stearate, microcrystalline cellulose, povidone, pregelatinized starch,
polyethylene glycol, silicon dioxide, stearic acid, itanium dioxide

May contain: FD&C lake black

Questions or comments?

Call toll free 1-888-952-0050 Monday through Friday

Package/Label Principal Display Panel

Cold Multi-symptom